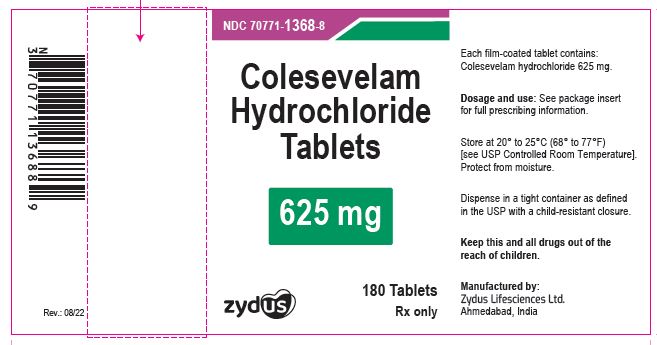 DRUG LABEL: COLESEVELAM
NDC: 70771-1368 | Form: TABLET
Manufacturer: Zydus Lifesciences Limited
Category: prescription | Type: HUMAN PRESCRIPTION DRUG LABEL
Date: 20241126

ACTIVE INGREDIENTS: COLESEVELAM HYDROCHLORIDE 625 mg/1 1
INACTIVE INGREDIENTS: AMMONIA; BUTYL ALCOHOL; CELLULOSE, MICROCRYSTALLINE; CROSPOVIDONE; FERRIC OXIDE RED; FERRIC OXIDE YELLOW; FERROSOFERRIC OXIDE; HYPROMELLOSE, UNSPECIFIED; ISOPROPYL ALCOHOL; MAGNESIUM STEARATE; METHACRYLIC ACID; POLYETHYLENE GLYCOL, UNSPECIFIED; POLYVINYL ALCOHOL, UNSPECIFIED; POVIDONE; PROPYLENE GLYCOL; SHELLAC; SILICON DIOXIDE; SODIUM BICARBONATE; TALC; TITANIUM DIOXIDE

COLESEVELAM HYDROCHLORIDE TABLETS

PACKAGE LABEL.PRINCIPAL DISPLAY PANEL

Colesevelam Hydrochloride Tablets, 625 mg

NDC 70771-1368-8

180 Tablets

Rx only